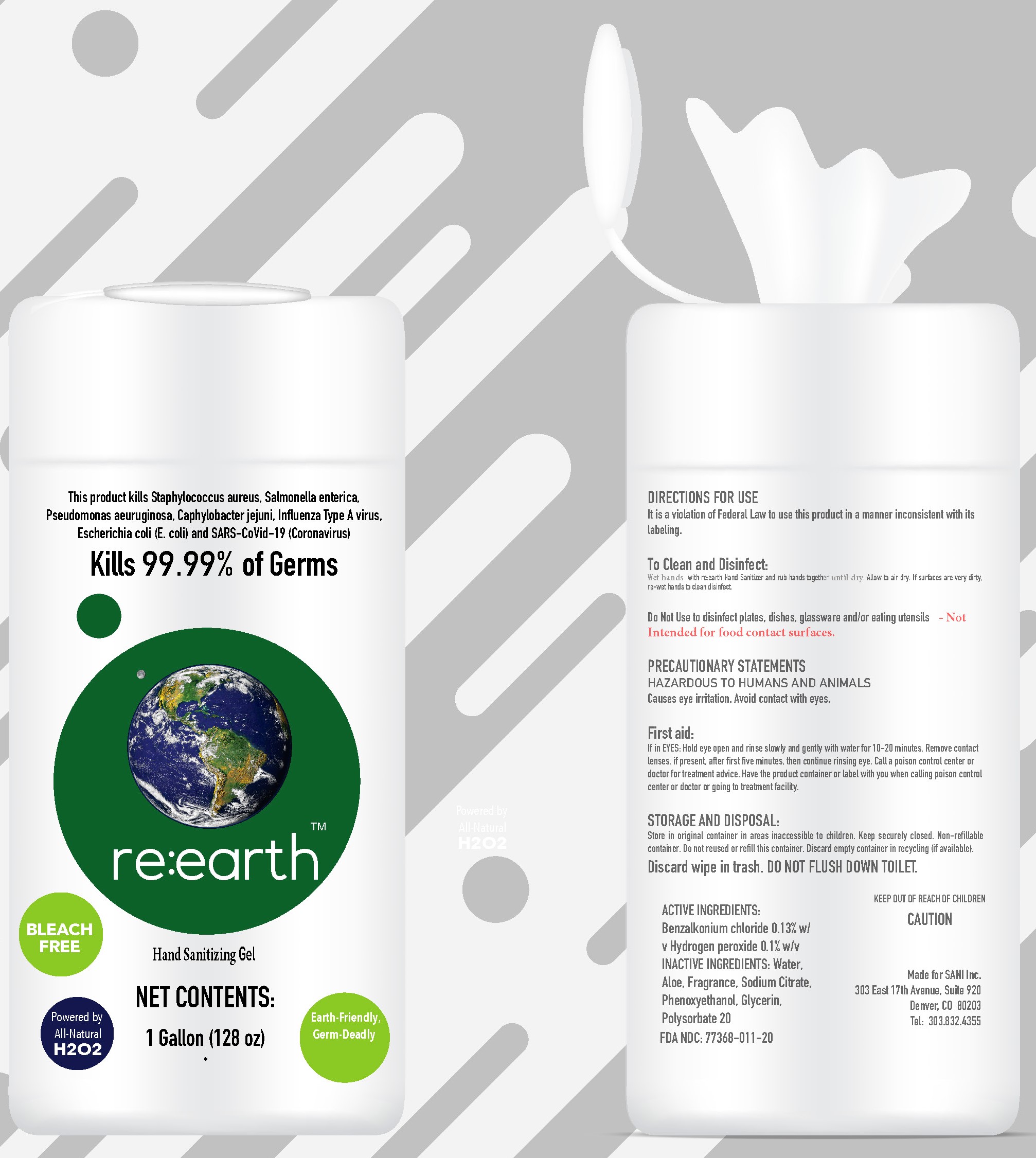 DRUG LABEL: reEarth Hand Sanitizer
NDC: 77368-022 | Form: GEL
Manufacturer: NuGenTec
Category: otc | Type: HUMAN OTC DRUG LABEL
Date: 20201014

ACTIVE INGREDIENTS: BENZALKONIUM CHLORIDE 1.3 mg/100 mL
INACTIVE INGREDIENTS: PHENOXYETHANOL 0.5 mL/100 mL; SODIUM CITRATE 0.05 mL/100 mL; ALOE 0.1 mL/100 mL; POLYSORBATE 20 0.2 mL/100 mL; GLYCERIN 1.45 mL/100 mL; HYDROGEN PEROXIDE 0.1 mL/100 mL; WATER

re:earth wipe Hand Sanitizer

Active Ingredient(s)

Benzalkonium Chloride 0.13%

hydrogen Peroxide.1%

Purpose

Antiseptic, Hand Sanitizer, Antibacterial

Use

Hand Sanitizer to help reduce bacteria that potentially can cause disease. For use when soap and water are not available.

Warnings

For external use only. Avoid Contact with Eyes.

Do not use

- in children less than 2 months of age
- on open skin wounds

When using this product keep out of eyes, ears, and mouth. In case of contact with eyes, rinse eyes thoroughly with water.
Stop use and ask a doctor if irritation or rash occurs. These may be signs of a serious condition.
Keep out of reach of children. If swallowed, get medical help or contact a Poison Control Center right away.

Stop use and ask a doctor if irritation or rash occurs. These may be signs of a serious condition.

Keep out of reach of children. If swallowed, get medical help or contact a Poison Control Center right away.

Directions

- Wet hands thoroughly with the product to cover all surfaces. Allow to dry without wiping.
- Supervise children under 6 years of age when using this product to avoid swallowing.

Other information

- Store between 0-40C (32-104F)
- Avoid freezing and excessive heat above 40C (104F)

Inactive ingredients

glycerin, purified water USP, Aloe, Fragrance, Sodium Citrate, Phenoxyethanol, Polysorbate 20

Package Label - Principal Display Panel

1 Gallon in Bottle NDC: 77368-022-01